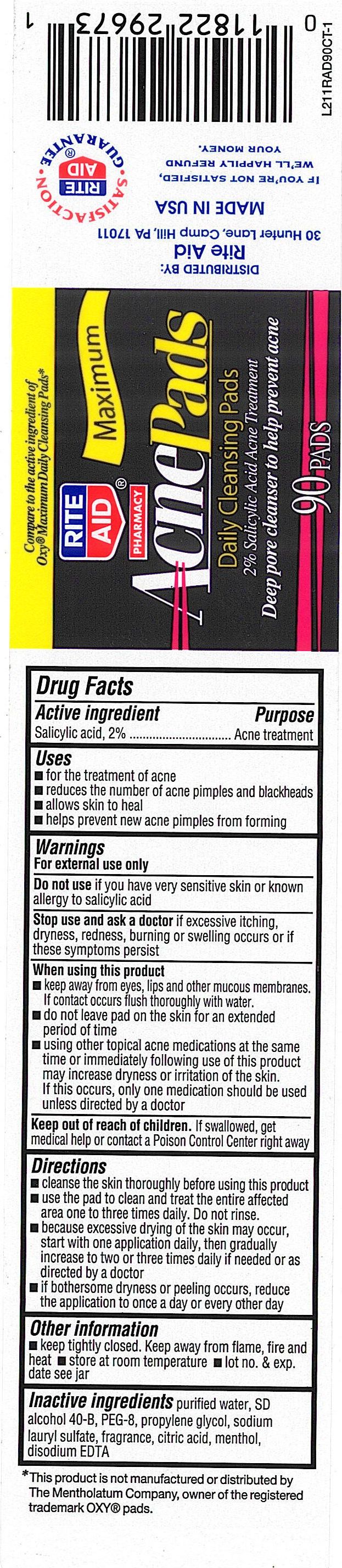 DRUG LABEL: Rite Aid Acne Pads, Daily Cleansing Pads
NDC: 11822-0414 | Form: SWAB
Manufacturer: Right Aid Corporation
Category: otc | Type: HUMAN OTC DRUG LABEL
Date: 20100713

ACTIVE INGREDIENTS: SALICYLIC ACID 21 mg/1 1
INACTIVE INGREDIENTS: WATER; DOCUSATE SODIUM; CARBOMER HOMOPOLYMER TYPE C; SODIUM HYDROXIDE; EDETATE SODIUM

drug facts

Active ingredient Purpose
Salicylic Acid, 2%.......................................Acne treatment

Uses
- for the treatment of acne
- reduces the number of acne pimples and blackheads
- allows skin to heal
- helps prevent new acne pimples from forming

Keep out of reach of children.If swallowed, get medical help or contact a Poison
Control Center right away.

Directions

- cleanse the skin thoroughly before using this product
- use the pad to clean and treat the entire affected area one to three times daily. Do not rinse.
- because excessive drying of the skin may occur - start with one application daily,
then gradually increase to two or three times daily if needed or as directed by a doctor.
- if bothersome dryness or peeling arise, reduce the application to once a day or every other day.
Other information
- keep tightly closed. Keep away from flame, fire and heat
- store at room temperature
- lot no. exp. date see jar

Warnings
For external use only.
Do not use if you have very sensitive skin or known allergy to salicylic acid
Stop use and ask a doctor if excessive itching, dryness redness burning
or swelling occurs or if these symptoms persist
When using this product
- keep away from eyes, lips and other mucous membranes. If contact occurs
flush thoroughly with water.
- do not leave pad on skin for an extended period of time
- using other topical acne medications at the same time or immediately following
use of this product may increase dryness or irritation of the skin. If this occurs,
only one medication should be used unless directed by a doctor
Keep out of reach of children. If swallowed, get medical help or contact a Poison
Control Center right away.

Directions

- cleanse the skin thoroughly before using this product
- use the pad to clean and treat the entire affected area one to three times daily. Do not rinse.
- because excessive drying of the skin may occur - start with one application daily,
then gradually increase to two or three times daily if needed or as directed by a doctor.
- if bothersome dryness or peeling arise, reduce the application to once a day or every other day.
Other information
- keep tightly closed. Keep away from flame, fire and heat
- store at room temperature
- lot no. exp. date see jar

INACTIVE INGREDIENT

Inactive Ingredients purified water, SD alcohol 40-B, PEG-8, propylene glycol,
sodium lauryl sulfate, fragrance, citric acid, menthol, disodium EDTA